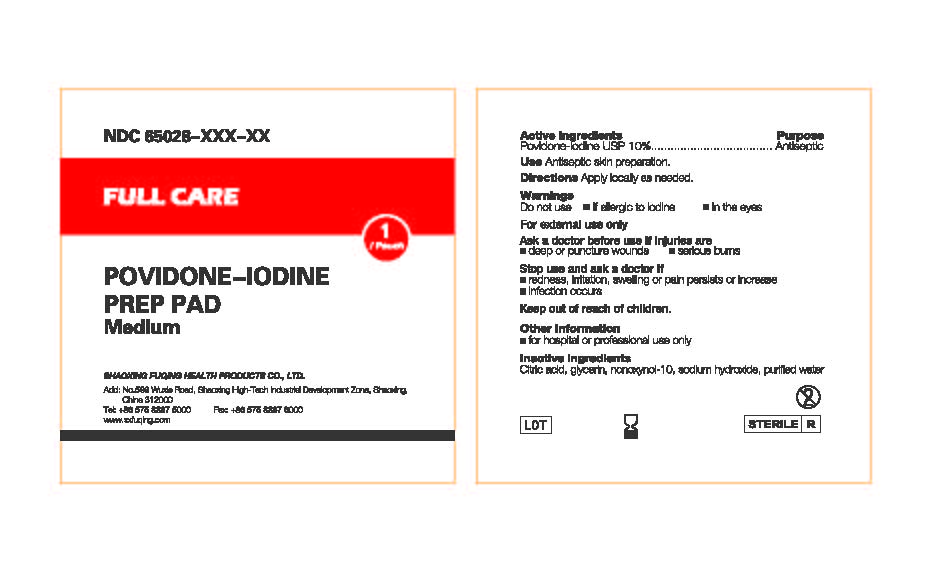 DRUG LABEL: Full Care  Povidone Iodine Prep Pad
NDC: 65028-007 | Form: SOLUTION
Manufacturer: Shaoxing Fuqing Health Products Co., Ltd.
Category: otc | Type: HUMAN OTC DRUG LABEL
Date: 20141108

ACTIVE INGREDIENTS: POVIDONE-IODINE 0.01 g/1 mL
INACTIVE INGREDIENTS: WATER; CITRIC ACID MONOHYDRATE; SODIUM HYDROXIDE; GLYCERIN; NONOXYNOL-10

Active Ingredient: Povidone-Iodine USP (10%)

Purpose: Antiseptic

INDICATIONS AND USAGE

Use: Antiseptic skin preparation

Warnings:

Do not use

- if allergic to iodine
- in the eyes

For external use only

Keep out of reach of children.

Ask a doctor before use if injuries are

- deep or puncture wounds
- serious burns

Stop use and ask a doctor if

- redness, irritation, swelling, or pain persists or increases
- infection occurs

DOSAGE AND ADMINISTRATION

Apply locally as need

Other information

- For hospital or professional use only

Inactive Ingredient

Citric Acid, Glycerin, Nonoxyol-10, Sodium Hydroxide, Purified Water